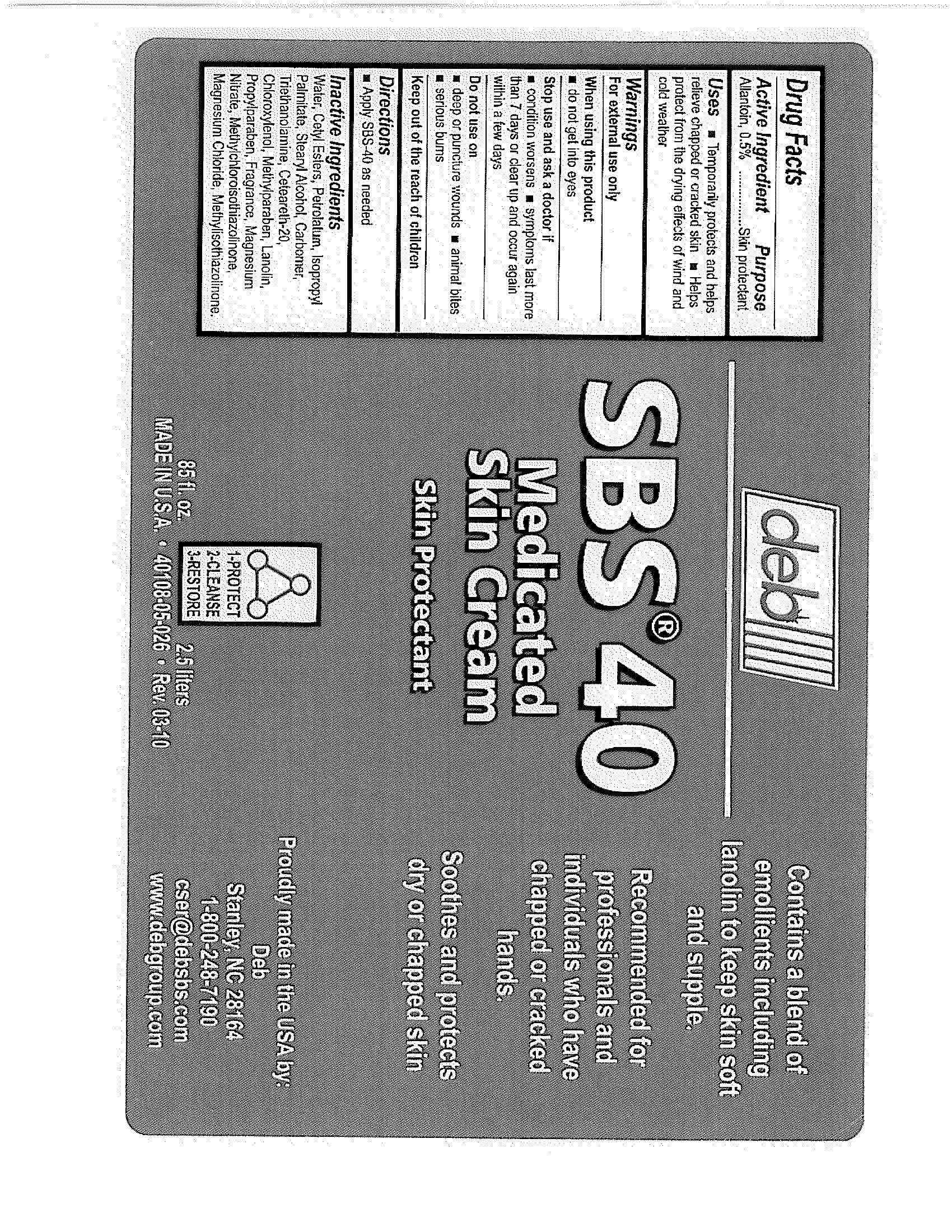 DRUG LABEL: SBS 40
NDC: 11084-040 | Form: LOTION
Manufacturer: Deb USA, Inc.
Category: otc | Type: HUMAN OTC DRUG LABEL
Date: 20100903

ACTIVE INGREDIENTS: Allantoin 0.5 mL/100  mL
INACTIVE INGREDIENTS: Cetyl Esters Wax; Petrolatum; Isopropyl Palmitate; Carbomer 934; Trolamine; Chloroxylenol; Methylparaben; Lanolin; Propylparaben; Stearyl Alcohol; POLYOXYL 20 CETOSTEARYL ETHER; METHYLCHLOROISOTHIAZOLINONE; METHYLISOTHIAZOLINONE; MAGNESIUM NITRATE; MAGNESIUM CHLORIDE; Water

Drug Facts

Active Ingredient

Allantoin, 0.5%

Purpose

Skin protectant

Uses

Temporarily protects and helps relieve chapped or cracked skin

Helps protect from the drying effects of wind and cold weather

Warnings

For external use only

When using this product do not get in eyes

Stop use and ask a doctor if

conditions worsen

symptoms last more than 7 days

or clear up and occur again within a few days

DO NOT USE

Enter section text here

Keep out of the reach of children

Directions

Apply SBS-40 as needed

Inactive Ingredients

Water, Cetyl Esters, Petrolatum, Isopropyl Palmitate, Stearyl Alcohol, Carbomer, Triethanolamine, Ceteareth-20, Chloroxylenol, Methylparaben, Lanolin, Propylparaben, Fragrance, Magnesium Nitrate, Methylchloroisothiazolinone, Magnesium Chloride, Methylisothiazolinone.

PACKAGE LABEL

deb

SBS 40

Medicated Skin Cream

Skin Protectant

1-Protect

2-Cleanse

3-Restore

85 fl. oz. 2.5 liters

Made in U.S.A.

40108-05-026

Contains a blend of emollients including lanolin to keep skin soft and supple.

Recommended for professionals and individuals who have chapped or cracker hands.

Soothes and protects dry or chapped skin